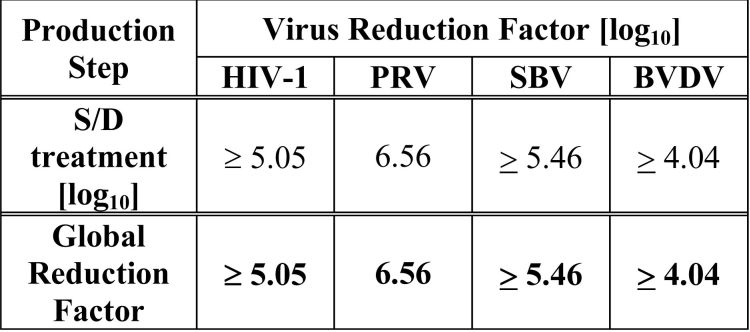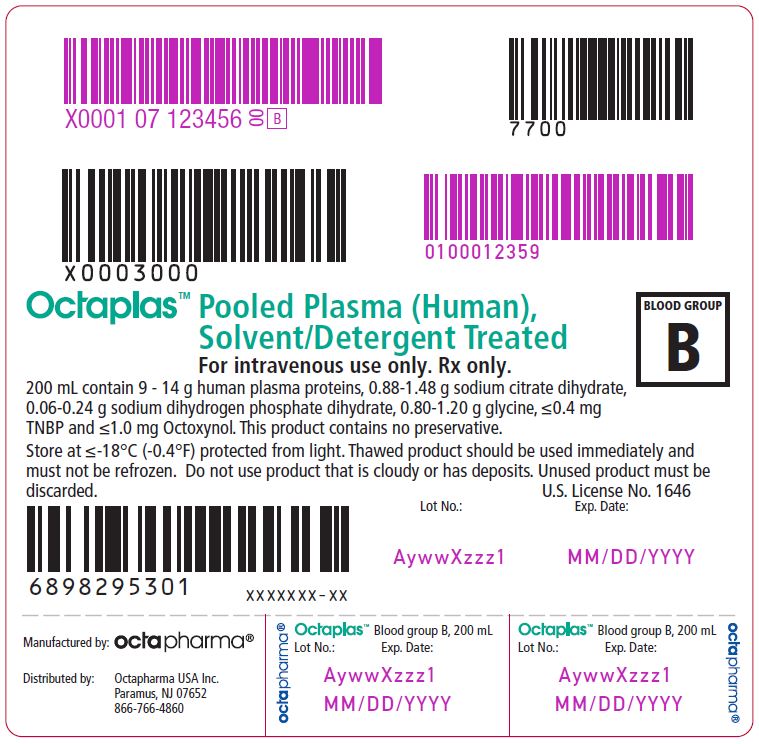 DRUG LABEL: Octaplas
NDC: 68982-953 | Form: SOLUTION
Manufacturer: Octapharma USA Inc
Category: other | Type: PLASMA DERIVATIVE
Date: 20241002

ACTIVE INGREDIENTS: PLASMA PROTEIN FRACTION (HUMAN) 11.5 g/200 mL

HIGHLIGHTS OF PRESCRIBING INFORMATION

These highlights do not include all the information needed to use Octaplas safely and effectively. See full prescribing information for Octaplas.
Octaplas, Pooled Plasma (Human), Solvent/Detergent treated Solution for Intravenous Infusion
Initial U.S. Approval: 2013

1 INDICATIONS AND USAGE

Octaplas is a solvent/detergent (S/D) treated, pooled human plasma indicated for

Replacement of multiple coagulation factors in patients with acquired deficiencies

due to liver disease

undergoing cardiac surgery or liver transplantation

Plasma exchange in patients with thrombotic thrombocytopenic purpura (TTP)

2 DOSAGE AND ADMINISTRATION

For intravenous use only.

Administer Octaplas based on AB0-blood group compatibility.

Indication | Dosage
Replacement of multiple coagulation factors in patients with acquired deficiencies | 10 to 15 milliliters per kg, Adjust the dose based on the desired clinical response
Plasma exchange in patients with TTP | 1 to 1.5 plasma volumes (40 to 60 milliliters per kg)

3 DOSAGE FORMS AND STRENGTHS

Solution for infusion containing 45 to 70 mg human plasma protein per mL in a 200 mL volume. (3)

4 CONTRAINDICATIONS

IgA deficiency

Severe deficiency of Protein S

History of hypersensitivity to fresh frozen plasma (FFP) or to plasma-derived products including any plasma protein

History of hypersensitivity reaction to Octaplas

5 WARNINGS AND PRECAUTIONS

Transfusion reactions can occur with ABO blood group mismatch (5.1)

High infusion rates can induce hypervolemia with consequent pulmonary edema or heart failure (5.2)

Excessive bleeding due to hyperfibrinolysis can occur due to low levels of alpha 2-antiplasmin (5.3)

Thrombosis can occur due to low levels of Protein S (5.4)

Citrate toxicity can occur with volumes exceeding one milliliter of Octaplas per kg per minute (5.5)

Octaplas is made from human blood and may carry the risk of transmitting infectious agents, e.g., viruses and theoretically, the variant Creutzfeldt-Jakob disease and Creutzfeldt-Jakob disease agent (5.6)

6 ADVERSE REACTIONS

The most common adverse reactions observed in ≥ 1% of patients included pruritis, urticaria, nausea, headache, paresthesia. (6).

Serious adverse reactions seen in clinical trials were anaphylactic shock, citrate toxicity and hypotension.

To report SUSPECTED ADVERSE REACTIONS, contact Octapharma USA Inc. at phone # 866-766-4860 or FDA at 1-800-FDA-1088 or www.fda.gov/medwatch.

FULL PRESCRIBING INFORMATION

1 INDICATIONS AND USAGE

Octaplas is a solvent / detergent (S/D) treated, pooled human plasma indicated for:

- Replacement of multiple coagulation factors in patients with acquired deficiencies
- due to liver disease
- undergoing cardiac surgery and liver transplantation
- Plasma exchange in patients with thrombotic thrombocytopenic purpura (TTP)

2 DOSAGE AND ADMINISTRATION

For intravenous use only

Administer Octaplas based on ABO-blood group compatibility.

2.1 Dose

Replacement of coagulation factors in patients with acquired deficiencies due to liver disease or undergoing cardiac surgery or liver transplant:

- Initially infuse of 10 to 15 mL Octaplas per kilogram body weight. This should increase the patient’s plasma coagulation factor levels by approximately 15-25%. If hemostasis is not achieved, use higher doses.
- Adjust dose based on desired clinical response.
- Monitor response, including measurement of activated partial thromboplastin time (aPTT), prothrombin time (PT) and/or specific coagulation factors.
- Plasma exchange in patients with TTP:
- Completely replace plasma volume removed during plasmapheresis with Octaplas. Generally, 1 to 1.5 plasma volumes correspond to 40 to 60 milliliters per kg.[ 1 , 2 ]

2.2 Administration

Administer Octaplas after thawing using an infusion set with a filter.

Octaplas should be inspected visually for particulate matter and discoloration prior to administration, whenever solution and container permit. Do not use if turbid.

Avoid shaking.

Steps for Thawing:

- For water bath:
- Thaw in the outer wrapper in a circulating water bath at +30°C to +37°C (86°F to 98.6°F). An overwrap bag may be used to provide further protection of contents if appropriate.
- Prevent water from contaminating the entry port.
- The minimum thawing time is 30 minutes at 37°C (98.6°F). The thawing time depends on the number of bags in the water bath. If more than one plasma bag is thawed in the same water bath, then the thawing time can be prolonged, but should not exceed 60 minutes.

- For dry tempering system:
- Place the Octaplas bags between the heating plates according to the manufacturer’s instructions.
- Thaw plasma following manufacturer directions between +30°C to +37°C (86°F to 98.6°F). Remove the product when the thawing process is completed. The thawing process may be monitored and recorded using the thawing device printer or barcode scanner recommended by the device manufacturer.
- Monitor the thawing process and record using the thawing device printer or barcode scanner recommended by the device manufacturer.

Do not freeze Octaplas. Discard unused product.

3 DOSAGE FORMS AND STRENGTHS

Solution for infusion containing 45 to 70 mg human plasma proteins per mL in a 200 mL volume.

4 CONTRAINDICATIONS

Do not use Octaplas in patients with:

- IgA deficiency
- Severe deficiency of Protein S
- History of hypersensitivity to fresh frozen plasma (FFP) or to plasma-derived products including any plasma protein
- History of hypersensitivity reaction to Octaplas

5 WARNINGS AND PRECAUTIONS

5.1 Transfusion reactions

Transfusion reactions can occur with ABO blood group mismatches. Administration of Octaplas must be based on ABO-blood group compatibility.

5.2 Hypervolemia

High infusion rates can induce hypervolemia with consequent pulmonary edema or heart failure. Monitor patients for signs and symptoms of pulmonary edema or heart failure and institute appropriate management.

5.3 Hyperfibrinolysis

Excessive bleeding due to hyperfibrinolysis can occur due to low levels of alpha 2-antiplasmin. Monitor for signs of excessive bleeding in patients undergoing liver transplantation.

5.4 Thrombosis

Thrombosis can occur due to low levels of Protein S. Monitor for signs and symptoms of thrombosis in patients at risk.

5.5 Citrate Toxicity

Citrate toxicity can occur with volumes exceeding one milliliter of Octaplas per kg per minute. The infusion rate should not exceed 0.020-0.025 mmol citrate per kilogram per minute (i.e., less than one milliliter Octaplas per kg per minute). Symptoms attributable to citrate toxicity (hypocalcemia) include fatigue, paresthesia and muscle spasms, especially in patients with liver function disorders. Administer calcium gluconate intravenously into another vein in order to minimize citrate toxicity.

5.6 Infection Risk from Human Plasma

Because Octaplas is made from human plasma, it may carry a risk of transmitting infectious agents, e.g., viruses, the variant Creutzfeldt-Jakob disease (vCJD) agent and theoretically, the Creutzfeldt-Jakob disease (CJD) agent. ALL infections suspected by a physician possibly to have been transmitted by this product should be reported by the physician or other healthcare provider to Octapharma [1-866-766-4860] or FDA at 1-800-FDA-1088 or www.fea.gov/medwatch. See Description (11)

6 ADVERSE REACTIONS

Serious adverse reactions seen in clinical trials were anaphylactic shock, citrate toxicity and severe hypotension.

The most common adverse reactions observed in ≥ 1% of subjects included pruritis, urticaria, nausea, headache and paresthesia.

6.1 Clinical Trials Experience

Because clinical trials are conducted under widely varying conditions, adverse reaction rates observed in clinical trials of a drug cannot be directly compared to rates in clinical trials of another drug and may not reflect rates observed in clinical practice.

Adverse reactions observed in clinical trials derive from 9 clinical trials. The mean dose administered ranged from 6 to 15 milliliters/kg body weight; when used in plasma exchange the dose was between 15 to 75 milliliters/kg. Two of the studies were conducted in healthy volunteers (n=90).

In total, 359 subjects received about 600 transfusion episodes in these trials.

The following table shows the adverse reactions observed in ≥ 1% of subjects in order of severity:

Nervous system disorders
Headache, paresthesia

Gastrointestinal disorders
Nausea

Skin and subcutaneous tissue disorders
Pruritis, urticaria

6.2 Postmarketing Experience

Because post-marketing reporting of adverse reactions is voluntary and from a population of uncertain size, it is not always possible to reliably estimate the frequency of these reactions or establish a causal relationship to product exposure.

Blood system disorders
Hyperfibrinolysis

Immune system disorders
Hypersensitivity reactions including anaphylactoid and allergic type of reactions

Metabolic and nutritional disorders
Alkalosis

Cardiovascular disorders
Cardiac arrest, circulatory overload, thromboembolism, tachycardia

Respiratory, thoracic and mediastinal disorders
Respiratory arrest or failure, bronchospasm, pulmonary edema, dyspnea, tachypnea, transfusion-related acute lung injury (TRALI)

Gastrointestinal disorders
Abdominal pain, vomiting

Skin and subcutaneous tissue disorders
Rash, erythema

General disorders and administration site conditions
Fever and/or chills, chest discomfort or pain

Investigations Seroconversions (passive transfer of antibodies); passive transmission of analytes, e.g. β-human chorionic gonadotropin [ 3 ]

Injury, poisoning and procedural complications
Citrate toxicity

7 DRUG INTERACTIONS

Do not inject drugs containing calcium in the same intravenous line with Octaplas because precipitants may block the line.

Passive transmission of analytes (e.g., β-human chorionic gonadotropin) may result in misleading positive results [ 3 ].

8 USE IN SPECIFIC POPULATIONS

8.1 Pregnancy

Risk Summary

Animal reproduction studies have not been conducted with Octaplas. It is not known whether Octaplas can cause fetal harm when administered to a pregnant woman or can affect reproduction capacity. Octaplas should be given to a pregnant woman only if clearly needed.

The background risk of major birth defects and miscarriage for the indicated population is unknown. In the U.S. general population, the estimated background risk of major birth defects and miscarriage in clinically recognized pregnancies is 2-4% and 15-20%, respectively [ 4 ].

8.2 Lactation

Risk Summary

Efficacy and safety of Octaplas in lactating women is unknown.

8.4 Pediatric Use

Octaplas was evaluated in 91 pediatric patients (age range 0-20 years) in two post-marketing requirement studies. Patients were dosed based on body weight and doses were adjusted as needed. There were no hyperfibrinolytic or treatment-related thromboembolic events reported by investigators. Please refer to Section 14 for information on clinical studies in the pediatric population.

8.5 Geriatric Use

Clinical studies of Octaplas did not include sufficient numbers of subjects aged 65 years and over to determine whether they respond differently from younger subjects. Other reported clinical experience has not identified differences in responses between the elderly and younger patients. In general, dose selection for an elderly patient should be cautious, usually starting at the low end of the dosing range, reflecting the greater frequency of decreased hepatic, renal, or cardiac function, and of concomitant disease or other drug therapy.

11 DESCRIPTION

Octaplas is a sterile frozen solution of solvent/detergent (S/D) treated pooled human plasma.

The active ingredient comprises plasma proteins such as albumin, immunoglobulins, other globulins, coagulation factors, complement proteins and protease inhibitors. The content and distribution of plasma proteins in Octaplas are comparable to reference ranges for healthy blood donors, except for Protein S and alpha 2-antiplasmin. Within a mean total protein content of 57 mg/mL, albumin comprises ~50% and immunoglobulin classes G, A, and M comprise ~12%, ~3% and ~1%, respectively. Protein S and alpha 2-antiplasmin, which are labile to S/D treatment, are controlled to ensure levels in the final product of ≥ 0.4 International Units (IU) per mL. Plasma lipids and lipoproteins are reduced due to S/D treatment and subsequent oil and solid phase extraction.

Composition of Octaplas

Component | Quantity per 200 mL dose
Human plasma proteins | 9.0 - 14.0 g
Sodium citrate dihydrate | 0.88 - 1.48 g
Sodium dihydrogen-phosphate dihydrate | 0.06 - 0.24 g
Glycine | 0.80 - 1.20 g

Octaplas is manufactured from human plasma collected in US licensed plasma donation centers. All plasma donations are tested for viral markers in compliance with US regulation. In addition, the manufacturing plasma pool may not contain a titer of human Parvovirus B19 DNA exceeding 10.0 IU per microliter and must have a negative result in a test for human Hepatitis E Virus (HEV) RNA by NAT PCR with a sensitivity of ≤ 2.5 log 10 IU/mL.

Each lot of Octaplas is manufactured from pooled plasma of a single ABO blood group (A, B, AB, or O). The manufacturing plasma pool is limited to 390 kg comprising 370-1,520 individual donations/units. Frozen plasma units are thawed and pooled. Sodium dihydrogen phosphate dihydrate is added as a buffer against increase in pH due to loss of CO 2 . After filtration through a 1 µm pore size membrane, the plasma pool is treated with S/D reagents [1% tri(n-butyl) phosphate (TNBP) and 1% Octoxynol for 1-1.5 hours at +30°C (86°F)] to inactivate enveloped viruses. The S/D reagents are removed by sequential oil and solid phase extraction procedures. Glycine is added to adjust the osmolality. Plasma with glycine is applied to a column filled with affinity ligand resin intended for selective binding of prion protein (PrP Sc). The effectiveness of this step in removal of prion infectivity from the product has not been established. After sterile filtration, the product is filled into sterile polyvinyl chloride blood bags, labeled, deep-frozen and stored at a temperature of ≤ -18°C (-0.4°F). The finished product is tested for coagulation factors II, V, VII, VIII, IX, X and XI, Protein C, Protein S, alpha 2-antiplasmin, fibrinogen and ADAMTS13.

The S/D treatment step has been validated to effectively inactivate relevant pathogenic and model enveloped viruses as summarized in Table 1.

Table 1 Virus Reduction During Octaplas Manufacture

HIV-1: Human Immunodeficiency Virus – 1

PRV: Pseudorabies Virus

SBV: Sindbis Virus

BVDV: Bovine Viral Diarrhea Virus

12 CLINICAL PHARMACOLOGY

12.1 Mechanism of Action

Octaplas replaces human plasma proteins.

12.2 Pharmacodynamics

Coagulation factor activities in the final product are controlled to obtain levels within the range of normal human plasma. Protein S and alpha 2-antiplasmin, which are labile to S/D treatment, are controlled to ensure levels in the final product of ≥ 0.4 International Units (IU) per mL.

13 NONCLINICAL TOXICOLOGY

13.1 Carcinogenesis, Mutagenesis, Impairment of Fertility

TNBP and Octoxynol used in the manufacturing process for viral inactivation may be present in the final product at levels not exceeding 2.0 µg/mL for TNBP and 5.0 µg/mL for Octoxynol.

Toxicity

No evidence of toxicity was observed for TNBP + Octoxynol in sub-acute toxicity studies. [ 5 ]

Mutagenicity

No evidence of mutagenicity was observed in in vitro or in vivo mutagenicity studies performed for TNBP. [ 6 - 11 ]

14 CLINICAL STUDIES

The Octaplas predecessor product was studied in healthy volunteers and in subjects with liver disease, liver transplantation, cardiac surgery and TTP.

A prospective, open-label, parallel group, non-randomized study was performed in surgical patients who were allocated to receive either a single infusion of Octaplas (N=20) or no plasma treatment (N=26) during open heart surgery.[ 12 ] A historical control group of patients who received standard single-donor FFP (N=20) was used to compare safety and efficacy. The average dose of Octaplas was 700 mL (range 200 to 3400 mL), compared with 1012 mL (range 500 to 4000 mL) for standard FFP. The choice of plasma product (Octaplas or FFP) did not appear to influence the postoperative course with respect to volume of postoperative bleeding, need for reoperation secondary to bleeding or length of postoperative hospital stay. This study was not powered to detect a difference in efficacy.

A prospective, single-blind, randomized study investigated the safety and efficacy of Octaplas compared with standard FFP in adult patients (N=55) with coagulopathy due to liver disease (LD) or liver transplantation (LTX), and for management of newly diagnosed thrombotic thrombocytopenic purpura (TTP).[ 13 - 15 ] Octaplas was infused in 13 of 24 patients with LD, 12 of 25 patients with LTX and all 3 patients with TTP. Within the LD and the LTX groups, patients were comparable in all clinical aspects and in the dose of plasma given. There were no relevant changes in any coagulation factors, but Protein C and fibrinogen improved in both groups, accompanied by a corresponding improvement in partial thromboplastin time (PTT) levels 24 hours after infusion. Similar degrees of correction of prolonged international normalized ratio (INR) and PTT values were achieved with both Octaplas and FFP. All 3 patients with TTP attained platelet counts of >50 x 10 ^9 /L by Day 10. This study was not powered to detect a difference in efficacy.

A prospective, open label, non-randomized study was conducted in postoperative open heart surgery patients (N=67) admitted to the surgical intensive care unit who were in need of plasma transfusion for acute bleeding or were at risk of bleeding; 36 patients received Octaplas (600 mL) and 31 received FFP (600 mL).[ 16 ] Measured parameters included PT, PTT, free Protein S and alpha 2-antiplasmin measured before treatment and 60 minutes after termination of plasma infusion. The decrease in PT and PTT and the rise in free Protein S were similar between the two study arms. Alpha 2-antiplasmin declined after Octaplas and remained unaffected by FFP. Clinical hemostasis evaluations were similar between the two treatment regimens. This study was not powered to detect a difference in efficacy.

A prospective, open-label, randomized, controlled, cross-over study in two groups (N=30 each) of healthy adult volunteers (mean age: 32.6±9.1 years) was carried out to show the relative recovery of coagulation factors and other hemostatic parameters after infusion of 1200 mL of Octaplas or the predecessor product, following a standard plasmapheresis of 600 mL. Coagulation factors (FI, FII, FV, FVII, FVIII, FIX, FX, and FXI) and hemostatic parameters (aPTT, PT and Protein C) were assessed post-infusion at 15 minutes, 2 hours and 24 hours. The primary objective was to demonstrate equivalence for recovery using a 10% margin. All coagulation and hemostatic parameters met the equivalence criterion. To verify the assumption of improvement in alpha 2-antiplasmin concentrations, a test for superiority was conducted. Statistically significant differences favoring Octaplas were found at 15 minutes (P=0.0012) and 2 hours (P=0.0190) post-transfusion in the per protocol population. Increased plasma levels of alpha 2-antiplasmin after infusion of Octaplas compared with the predecessor product may result from increased concentrations of this plasmin inhibitor found in Octaplas.

A prospective, open-label, multicenter, single arm, postmarketing study was conducted to investigate the safety, tolerability and efficacy of Octaplas in the management of pediatric patients requiring replacement of multiple coagulation factors. A total of 50 patients [37 neonates/infants (0 to 2 years old) and 13 children and adolescents (> 2 to 16 years old)] requiring cardiac surgery (N=40), liver transplantation and/or with liver dysfunction (N=5), sepsis-related coagulopathy (N=4) and hypoxic encephalopathy (N=1) were included in the study. There were no hyperfibrinolytic or treatment-related thromboembolic events reported by investigators. The investigators’ overall safety assessment was prospectively defined as excellent (treatment was well tolerated by the patient), moderate (adverse reactions were observed, but easily resolved or not clinically significant) or poor (adverse reactions were observed requiring significant medical intervention) to describe the patient’s experience with Octaplas. Overall safety was assessed by investigators as ”excellent” for all 50 patients. Hemostatic parameters as measured by INR, PT, aPTT, thromboelastography (TEG) or thromboelastometry (TEM) were within expected ranges following use of Octaplas.

A prospective, open-label, multicenter, single-arm, postmarketing study assessed the safety and tolerability of Octaplas in the management of subjects who underwent therapeutic plasma exchange (TPE). A total of 102 TPE procedures were performed in 41 subjects aged 2 to 20 years [young children: Group 1 (age 2 to <12): N=15; adolescents: Group 2 (12 to <17): N=13; and young adults: Group 3 (≥17): N=13]. Overall, a total of 135,137 mL of Octaplas was administered. The underlying disease category for these subjects included immune system disorders (N=14), nervous system disorders (N=12), renal and urinary disorders (N=8), infections and infestations (N=4), and other disorders (N=3). Each subject underwent between 1 and 6 TPEs (mean: 2.5 TPEs). The actual dose administered per TPE ranged from 4 mL/kg to 72 mL/kg (mean: 28.6 mL/kg), with a mean total volume administered per TPE of 1325 mL (range: 113 mL to 4000 mL). Infusion rates (mean) were similar across age groups (0.32 mL/kg/min to 0.41 mL/kg/min). No thrombotic or thromboembolic events were found in any study subject. In total, 8 adverse reactions were found in 4 subjects (9.8%). These included 5 adverse reactions in three adolescents (4 in TPE #1 and 1 in TPE #4) and 3 adverse reactions in one young adult (2 in TPE #1 and 1 in TPE #2). Adverse reactions in adolescents included citrate toxicity (2 in 2 subjects), and headache, pyrexia, and urticaria (each reported in 1 subject), while adverse reactions found in young adults included inflammatory marker (C-reactive protein, procalcitonin) increased, myalgia, and nausea (each reported in 1 subject). Most (7/8) adverse reactions were mild in intensity and recovered/resolved by end of study. No treatment-related serious adverse events were reported. Overall safety was assessed by investigators as excellent for most subjects (>90%) at 24 hours after each TPE throughout the study using prespecified definitions of excellent, good and poor.

15 REFERENCES

1. Hellstern, P., et al. "Practical guidelines for the clinical use of plasma." Thromb Res. 107 Suppl 1 (2002): S53-S57.
2. Scully, M., et al. "Guidelines on the diagnosis and management of thrombotic thrombocytopenic purpura and other thrombotic microangiopathies." British Journal of Haematology 158.3 (2012): 323-35.
3. Jilma-Stohlawetz P, et al. "False-positive pregnancy test after transfusion of solvent/detergent-treated plasma. " Transfusion 57.12 (2017): 2965–8.
4. FDA Briefing Document Risk Communication Advisory Committee Meeting March 5-6, 2018. Communicating Information about Risks in Pregnancy in Product Labeling for Patients and Providers to Make Informed Decisions about the Use of Drugs during Pregnancy
5. Horowitz B: Potential accumulation of tri(n-butyl)phosphate in solvent-detergent virus-inactivated plasma products. Transfusion 1991;31:871
6. Hanna PJ, Dyer KF: Mutagenicity of organophosphorus compounds in bacteria and Drosophila. Mutat.Res. 1975;28:405-420
7. Batt KJ, Healy CE, Kneiss JJ, et al: Genotoxicity testing of tributyl phosphate. – 1992
8. Wangenheim J, Bolcsfoldi G: Mouse lymphoma L5178Y thymidine kinase locus assay of 50 compounds. Mutagenesis 1988;3:193-205
9. Assinder SJ, Upshall A: Paramorphogenic and genotoxic activity of Triton X-100 and sodium dodecyl sulphate in Aspergillus nidulans. Mutat.Res. 1985;142:179-181
10. Buttar HS, Swierenga SH, Matula TI: Evaluation of the cytotoxicity and genotoxicity of the spermicides nonoxynol-9 and octoxynol-9. Toxicol.Lett. 1986;31:65-73
11. Auletta CS, Kotkoskie LA, Saulog T, et al: A dietary oncogenicity study of tributyl phosphate in the CD-1 mouse. Toxicology 1998;128:135-14
12. Solheim, B. G. et al. "The Use of OCTAPLAS in Patients Undergoing Open Heart Surgery." DIC: Pathogenesis, Diagnosis and Therapy of Disseminated Intravascular Fibrin Formation. Ed. G. Müller-Berghaus and et al. Elsevier Science Publishers B.V., Netherlands, 1993. 253-62.
13. Evans, G., et al. "Solvent/detergent fresh frozen plasma as primary treatment of acute thrombotic thrombocytopenic purpura." Clin Lab Haematol 21.2 (1999): 119-23.
14. Freeman, J. W., et al. "A randomized trial of solvent/detergent and standard fresh frozen plasma in the treatment of the coagulopathy seen during Orthotopic Liver Transplantation." Vox Sang 74 Suppl 1 (1998): 225-29.
15. Williamson, L. M., et al. "A randomized trial of solvent/detergent-treated and standard fresh-frozen plasma in the coagulopathy of liver disease and liver transplantation." Transfusion 39.11-12 (1999): 1227-34.
16. Haubelt, H., et al. "Effects of solvent/detergent-treated plasma and fresh-frozen plasma on haemostasis and fibrinolysis in complex coagulopathy following open- heart surgery." Vox Sang 82.1 (2002): 9-14.

16 HOW SUPPLIED/STORAGE AND HANDLING

Octaplas is supplied in polyvinyl chloride blood bags containing 200 mL frozen solution and has a slightly yellow appearance.

NDC Number | Blood group
68982-952 - 01 | Blood group A
68982-953 - 01 | Blood group B
68982-954 - 01 | Blood group AB
68982-955 - 01 | Blood group 0

Storage and Handling

- Store at ≤ -18°C (-0.4°F) for 3 years from the date of manufacture.
- Store protected from light.
- Thaw product according to instructions in section 2.2.
- Use thawed product within 24 hr. if stored at 1 - 6°C (33.8°F to 42.8°F) or within 8 hr. if stored at 20 - 25°C (68°F to 77°F).
- Do not refreeze thawed product.
- Do not use product that is cloudy or has deposits.
- Discard product after the expiration date printed on the container label.

17 PATIENT COUNSELING INFORMATION

Inform patients to report:

- Early signs of hypersensitivity reactions including hives, generalized urticaria, tightness of the chest, wheezing, hypotension, or anaphylaxis.
- Development of edema or volume overload including shortness of breath or breathing difficulties

Remind patients that Octaplas is made from human blood and may contain infectious agents that can cause disease. Report flu-like or other symptoms or viral infection.

Manufactured by:

Octapharma AB

Lars Forssells gata 23

SE- 112 75, Sweden

U.S. License No. 1646

Distributed by:

Octapharma USA Inc.

117 West Century Road

Paramus, NJ 07652

18 PACKAGE LABEL - PRINCIPAL DISPLAY PANEL

solvent/detergent (S/D) treated human plasma

Octapharma Pharmazeutika Produktionsges.m.b.H

Blood group B

NDC 68982-953 – 01